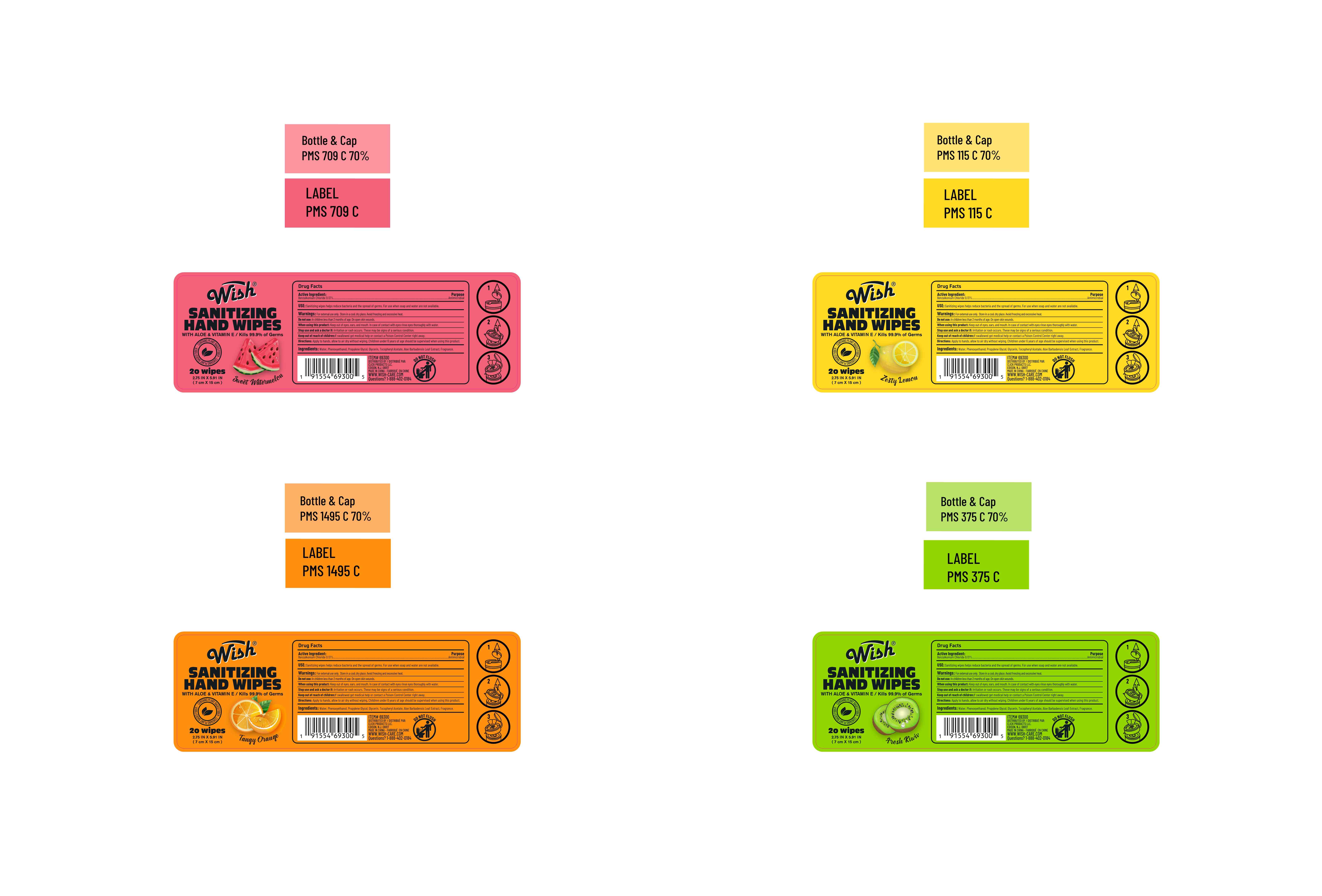 DRUG LABEL: SANITIZING HAND WIPES
NDC: 75181-010 | Form: CLOTH
Manufacturer: Jinhua Aidi Daily Chemical Co., Ltd.
Category: otc | Type: HUMAN OTC DRUG LABEL
Date: 20250819

ACTIVE INGREDIENTS: BENZALKONIUM CHLORIDE 0.13 g/100 g
INACTIVE INGREDIENTS: .ALPHA.-TOCOPHEROL ACETATE, D-; PROPYLENE GLYCOL; ALOE BARBADENSIS LEAF; GLYCERIN; PHENOXYETHANOL; WATER

SANITIZING HAND WIPES 20wipes

Active Ingredient(s)

Benzalkonium Chloride 0.13%

Purpose

Antimicrobial Agent

Use

Sanitizing wipes helps reduce bacteria and the spread of germs. For use when soap and water are not available.

Warnings

For external use only. Store in a cool, dry place. Avoid freezing and excessive heat.

Do not use: In children less than 2 months of age. On open skin wounds.

When using this product: Keep out of eves, ears, and mouth. in case of contact with eyes rinse eyes thoroughly with water.

Stop use and ask a doctor if: lrritation or rash occurs. These may be sians of a serious condition.

Keep out of reach of children:lf swallowed get medical help or contact a Poison Control Center right away.

Directions

Apply to hands, allow to ar dry without wiping. childiren under 6 vears of ace should be supervised when using this product.

Other information

Store in a cool, dry place.

Avoid freezing and excessive heat.

Inactive ingredients

Water, Phenoxyethanol, Propylene Glycol, Glycerin, Tocopheryl Acetate, Aloe Barbadensis Leaf Extract, Fragrance.

Package Label - Principal Display Panel

20 wipes in 1 bottle NDC: 75181-010-01